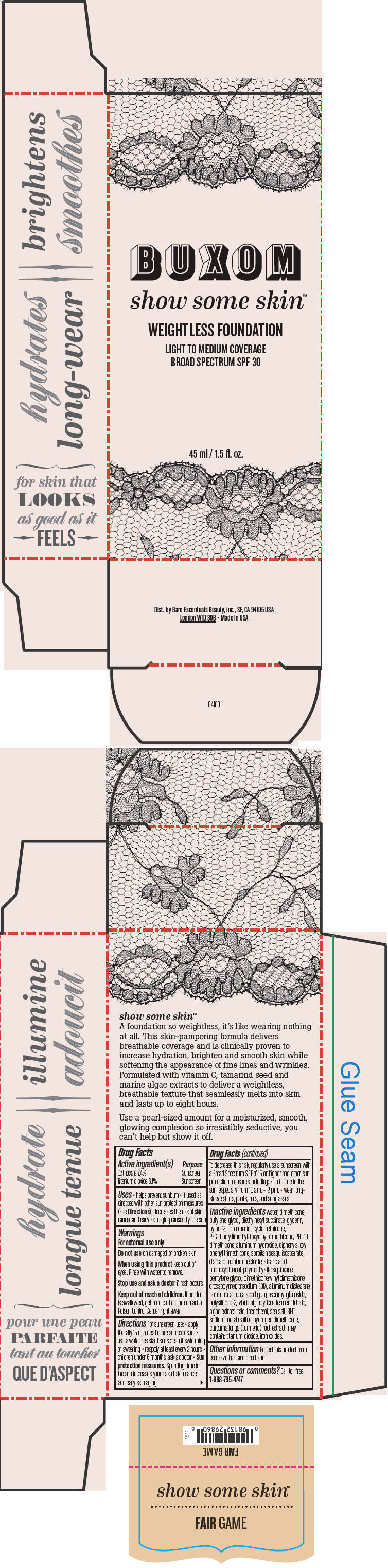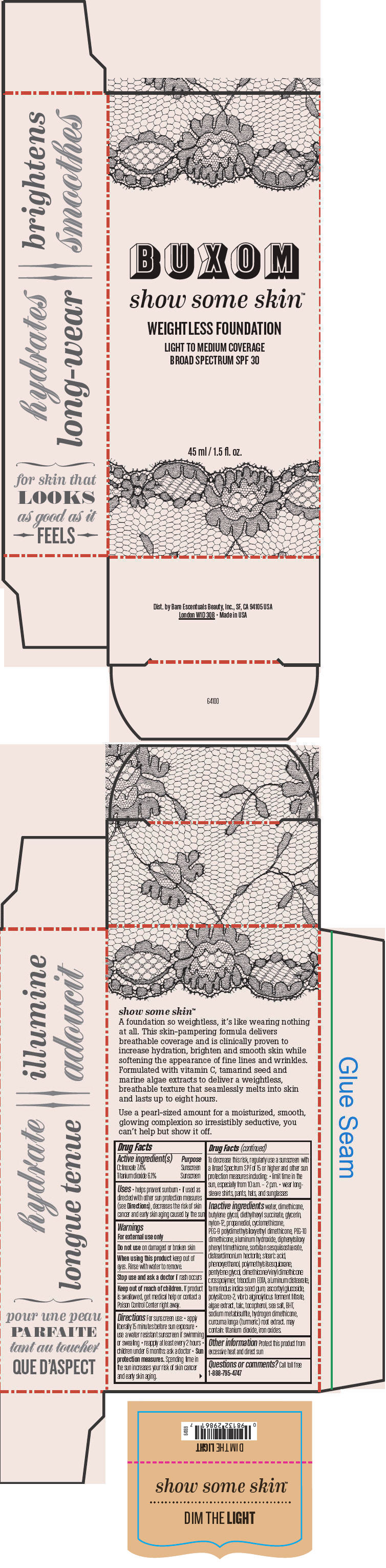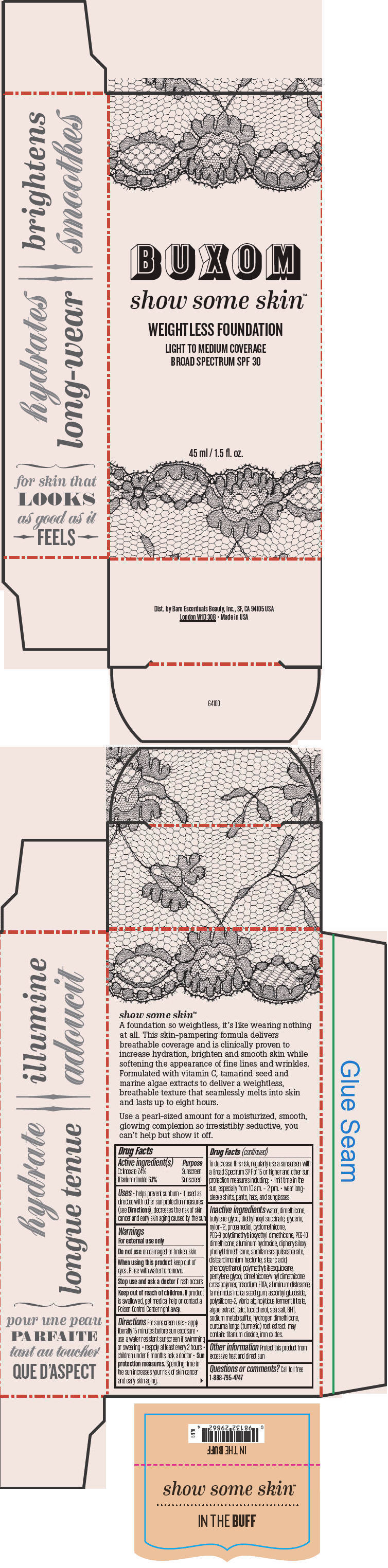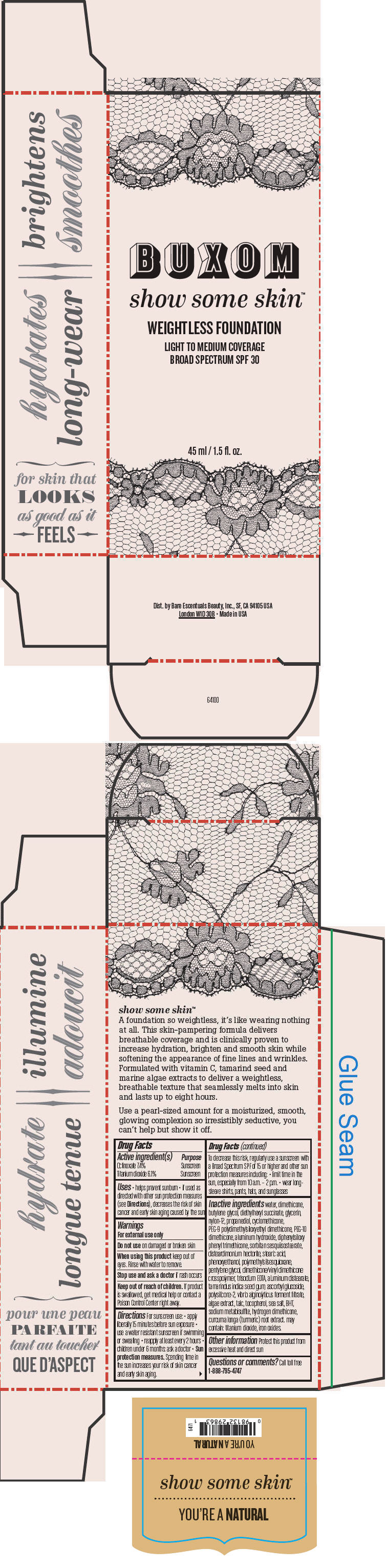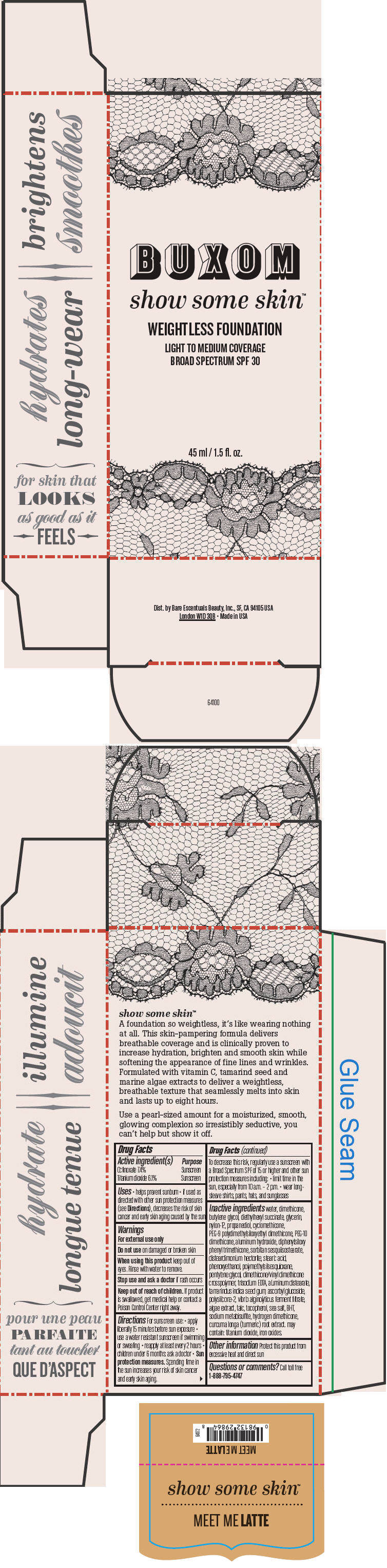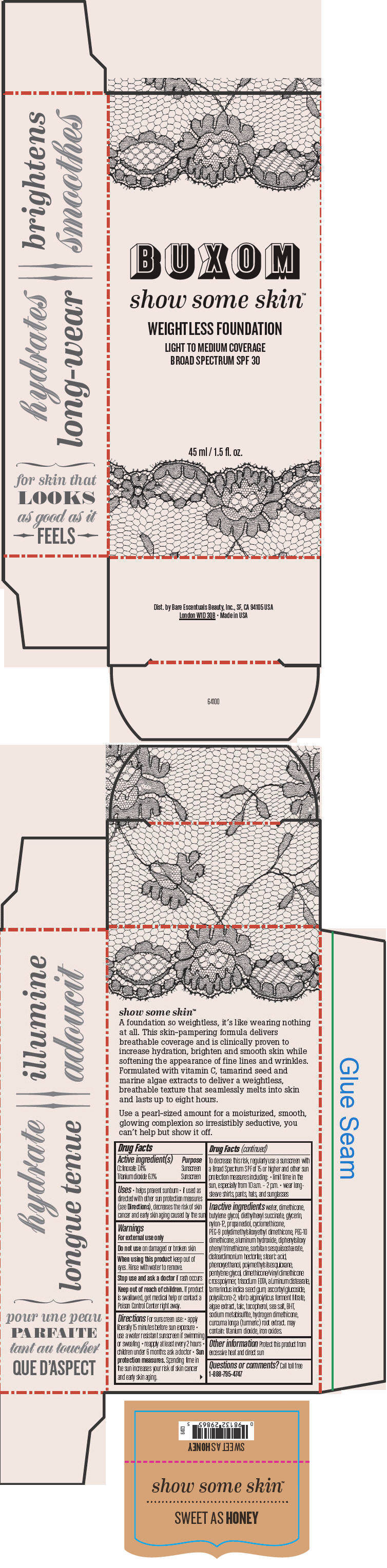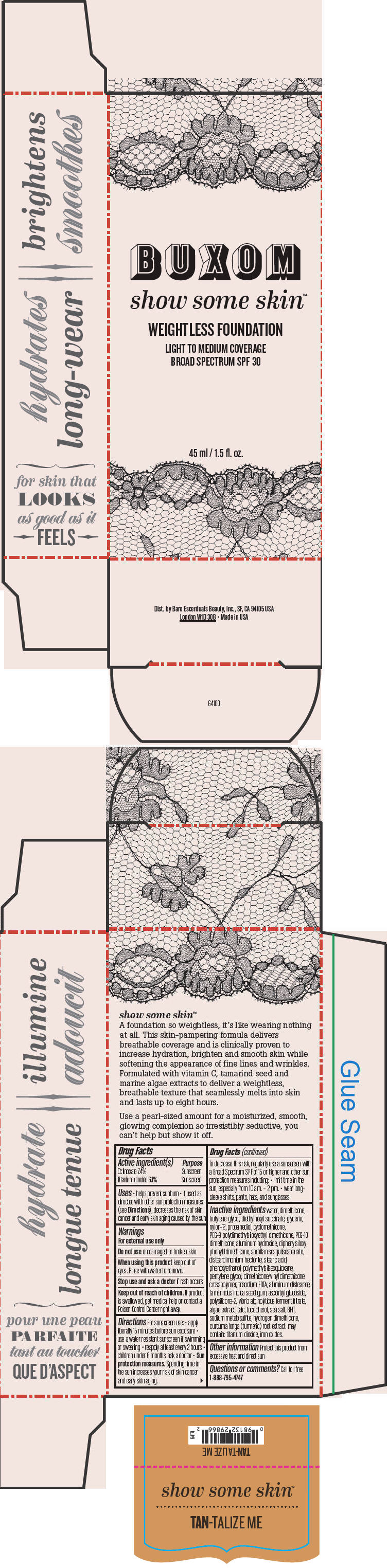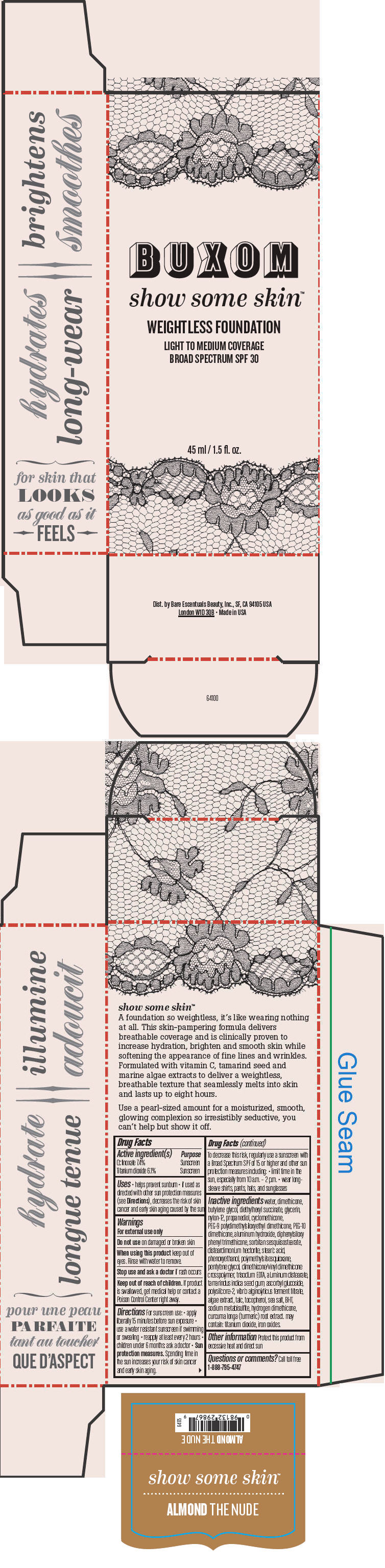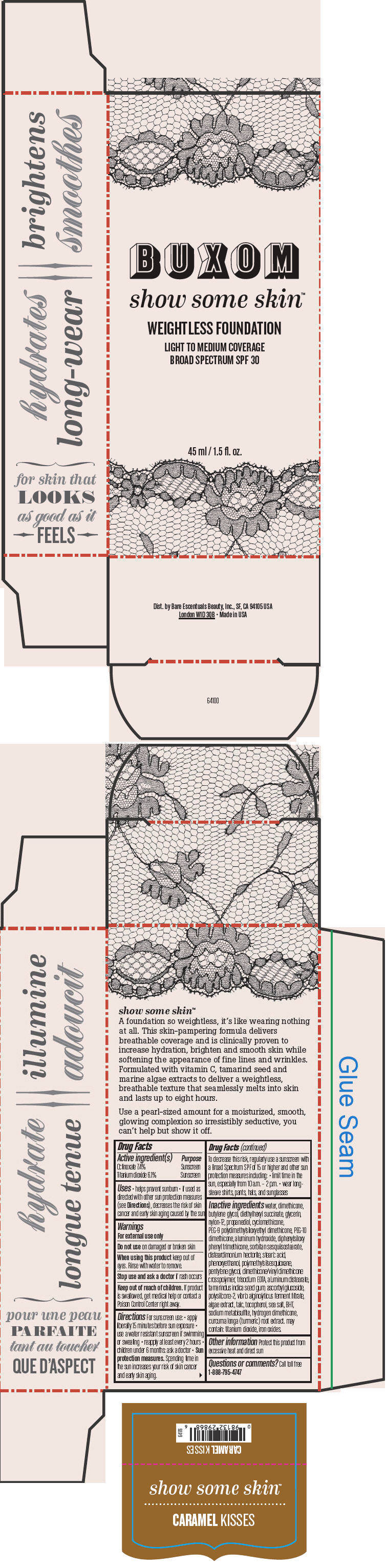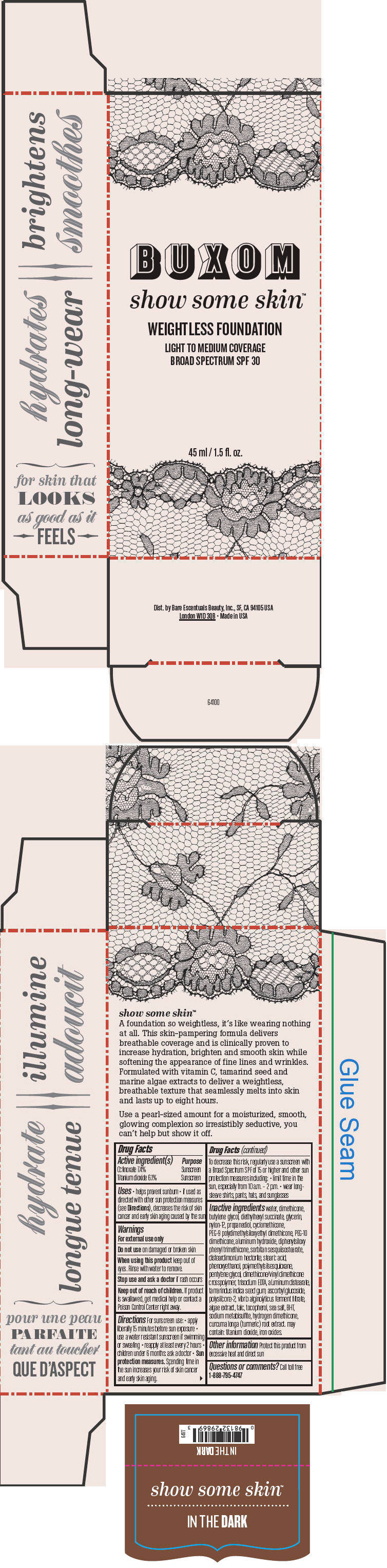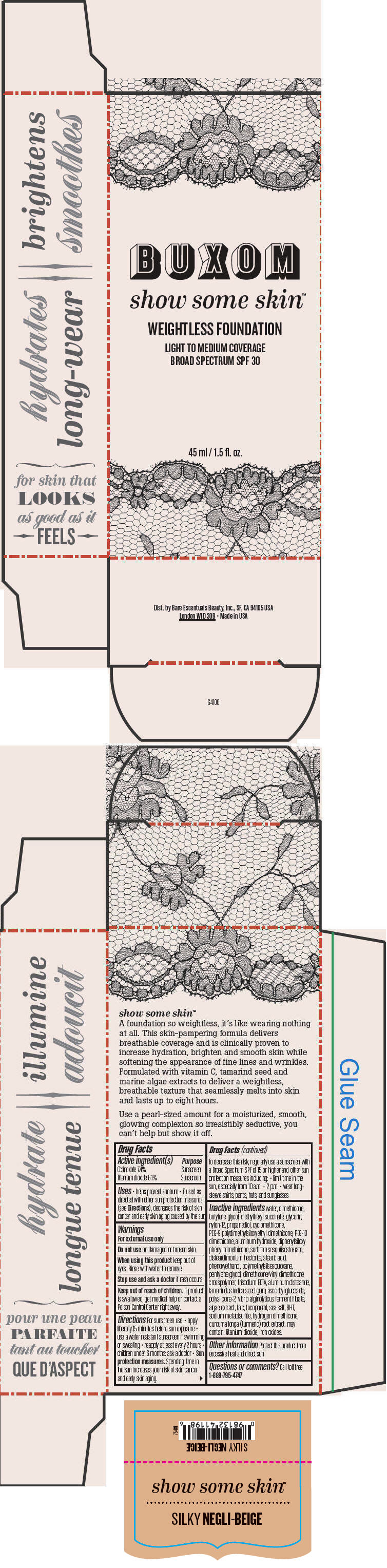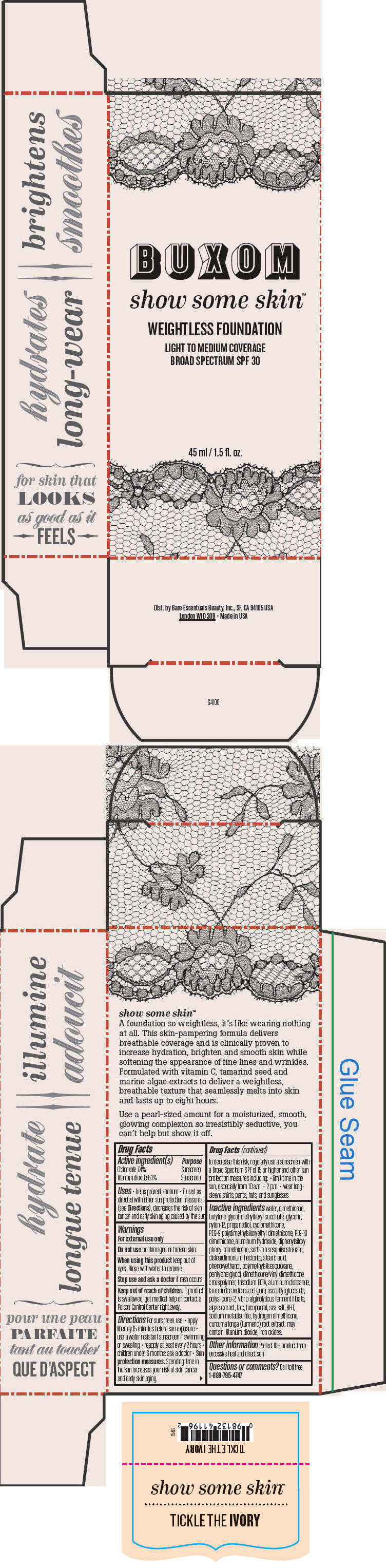 DRUG LABEL: Buxom Show Some Skin Weightless Foundation Broad Spectrum SPF 30 
NDC: 98132-710 | Form: LIQUID
Manufacturer: Bare Escentuals Beauty, Inc.
Category: otc | Type: HUMAN OTC DRUG LABEL
Date: 20150605

ACTIVE INGREDIENTS: Octinoxate 74 mg/1 mL; Titanium Dioxide 61 mg/1 mL
INACTIVE INGREDIENTS: water; dimethicone; butylene glycol; diethylhexyl succinate; glycerin; nylon-12; propanediol; cyclomethicone; PEG-9 polydimethylsiloxyethyl dimethicone; aluminum hydroxide; diphenylsiloxy phenyl trimethicone; disteardimonium hectorite; stearic acid; phenoxyethanol; pentylene glycol; edetate trisodium; aluminum distearate; tamarind seed; ascorbyl glucoside; talc; tocopherol; sea salt; butylated hydroxytoluene; sodium metabisulfite; turmeric; ferric oxide red

Buxom Show Some Skin™ Weightless Foundation Broad Spectrum SPF 30

Drug Facts

ACTIVE INGREDIENT

Active ingredient(s) | Purpose
Octinoxate 7.4% | Sunscreen
Titanium dioxide 6.1% | Sunscreen

Uses

- helps prevent sunburn
- if used as directed with other sun protection measures (see Directions), decreases the risk of skin cancer and early skin aging caused by the sun

Warnings

For external use only

Do not use on damaged or broken skin

When using this product keep out of eyes. Rinse with water to remove.

Stop use and ask a doctor if rash occurs

Keep out of reach of children. If product is swallowed, get medical help or contact a Poison Control Center right away.

Directions

For sunscreen use:

- apply liberally 15 minutes before sun exposure
- use a water resistant sunscreen if swimming or sweating
- reapply at least every 2 hours
- children under 6 months: ask a doctor

- Sun protection measures. Spending time in the sun increases your risk of skin cancer and early skin aging.

To decrease this risk, regularly use a sunscreen with a Broad Spectrum SPF of 15 or higher and other sun protection measures including:

- limit time in the sun, especially from 10 a.m. – 2 p.m.
- wear long-sleeve shirts, pants, hats, and sunglasses

Inactive ingredients

water, dimethicone, butylene glycol, diethylhexyl succinate, glycerin, nylon-12, propanediol, cyclomethicone, PEG-9 polydimethylsiloxyethyl dimethicone, PEG-10 dimethicone, aluminum hydroxide, diphenylsiloxy phenyl trimethicone, sorbitan sesquiisostearate, disteardimonium hectorite, stearic acid, phenoxyethanol, polymethylsilsesquioxane, pentylene glycol, dimethicone/vinyl dimethicone crosspolymer, trisodium EDTA, aluminum distearate, tamarindus indica seed gum, ascorbyl glucoside, polysilicone-2, vibrio alginolyticus ferment filtrate, algae extract, talc, tocopherol, sea salt, BHT, sodium metabisulfite, hydrogen dimethicone, curcuma longa (turmeric) root extract. may contain: titanium dioxide, iron oxides.

Other information

Protect this product from excessive heat and direct sun

Questions or comments?

Call toll free 1-888-795-4747

Dist. by Bare Escentuals Beauty, Inc., SF, CA 94105 USA

PRINCIPAL DISPLAY PANEL - 45 ml Tube Box - Fair Game

BUXOM

show some skin™

WEIGHTLESS FOUNDATION

LIGHT TO MEDIUM COVERAGE
BROAD SPECTRUM SPF 30

45 ml / 1.5 fl. oz.

PRINCIPAL DISPLAY PANEL - 45 ml Tube Box - Dim The Light

BUXOM

show some skin™

WEIGHTLESS FOUNDATION

LIGHT TO MEDIUM COVERAGE
BROAD SPECTRUM SPF 30

45 ml / 1.5 fl. oz.

PRINCIPAL DISPLAY PANEL - 45 ml Tube Box - In The Buff

BUXOM

show some skin™

WEIGHTLESS FOUNDATION

LIGHT TO MEDIUM COVERAGE
BROAD SPECTRUM SPF 30

45 ml / 1.5 fl. oz.

PRINCIPAL DISPLAY PANEL - 45 ml Tube Box - You're A Natural

BUXOM

show some skin™

WEIGHTLESS FOUNDATION

LIGHT TO MEDIUM COVERAGE
BROAD SPECTRUM SPF 30

45 ml / 1.5 fl. oz.

PRINCIPAL DISPLAY PANEL - 45 ml Tube Box - Meet Me Latte

BUXOM

show some skin™

WEIGHTLESS FOUNDATION

LIGHT TO MEDIUM COVERAGE
BROAD SPECTRUM SPF 30

45 ml / 1.5 fl. oz.

PRINCIPAL DISPLAY PANEL - 45 ml Tube Box - Sweet As Honey

BUXOM

show some skin™

WEIGHTLESS FOUNDATION

LIGHT TO MEDIUM COVERAGE
BROAD SPECTRUM SPF 30

45 ml / 1.5 fl. oz.

PRINCIPAL DISPLAY PANEL - 45 ml Tube Box - Tan-Talize Me

BUXOM

show some skin™

WEIGHTLESS FOUNDATION

LIGHT TO MEDIUM COVERAGE
BROAD SPECTRUM SPF 30

45 ml / 1.5 fl. oz.

PRINCIPAL DISPLAY PANEL - 45 ml Tube Box - Almond The Nude

BUXOM

show some skin™

WEIGHTLESS FOUNDATION

LIGHT TO MEDIUM COVERAGE
BROAD SPECTRUM SPF 30

45 ml / 1.5 fl. oz.

PRINCIPAL DISPLAY PANEL - 45 ml Tube Box - Caramel Kisses

BUXOM

show some skin™

WEIGHTLESS FOUNDATION

LIGHT TO MEDIUM COVERAGE
BROAD SPECTRUM SPF 30

45 ml / 1.5 fl. oz.

PRINCIPAL DISPLAY PANEL - 45 ml Tube Box - In The Dark

BUXOM

show some skin™

WEIGHTLESS FOUNDATION

LIGHT TO MEDIUM COVERAGE
BROAD SPECTRUM SPF 30

45 ml / 1.5 fl. oz.

PRINCIPAL DISPLAY PANEL - 45 ml Tube Box - Silky Negli-Beige

BUXOM

show some skin™

WEIGHTLESS FOUNDATION

LIGHT TO MEDIUM COVERAGE
BROAD SPECTRUM SPF 30

45 ml / 1.5 fl. oz.

PRINCIPAL DISPLAY PANEL - 45 ml Tube Box - Tickle The Ivory

BUXOM

show some skin™

WEIGHTLESS FOUNDATION

LIGHT TO MEDIUM COVERAGE
BROAD SPECTRUM SPF 30

45 ml / 1.5 fl. oz.